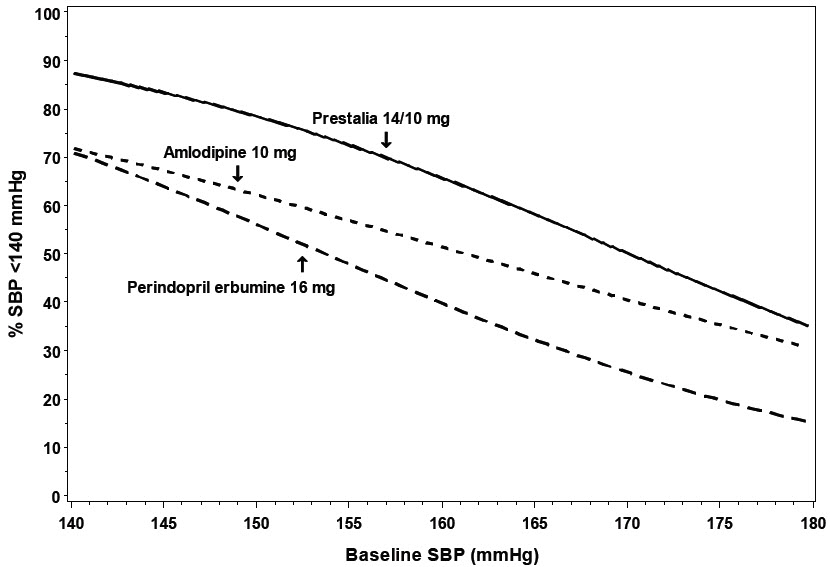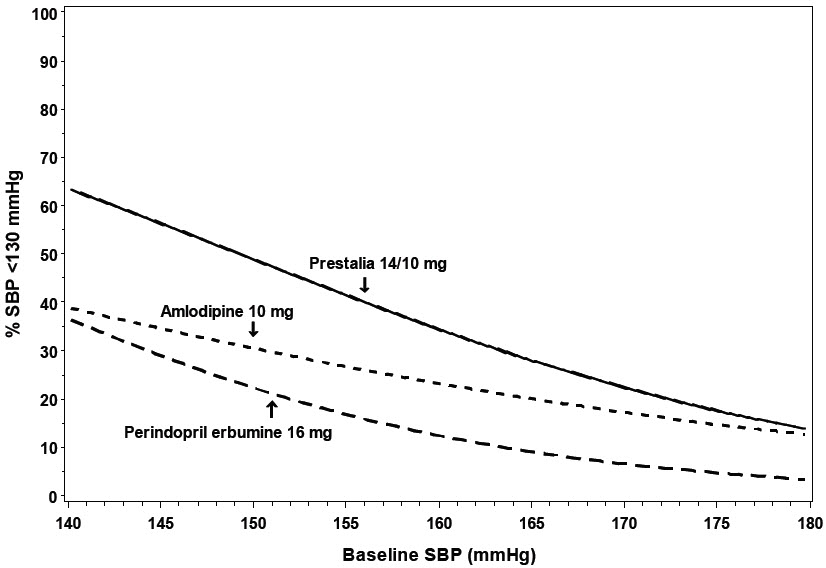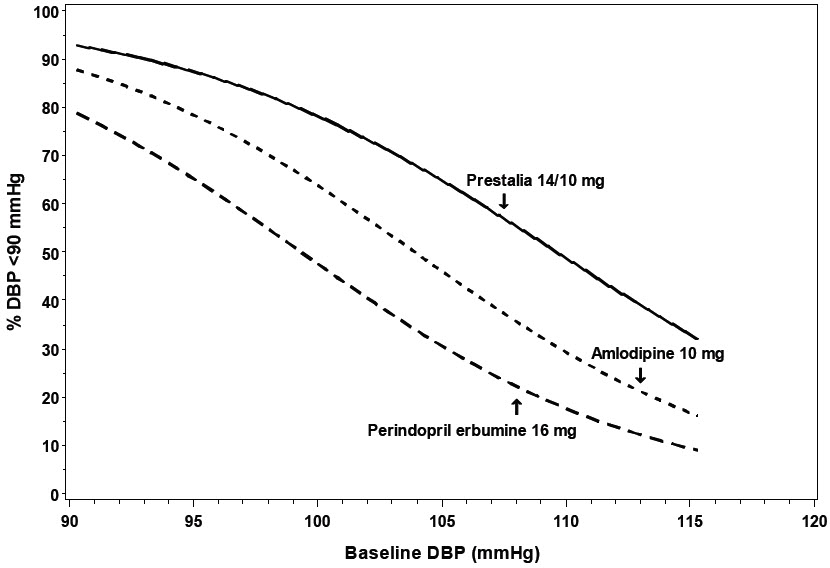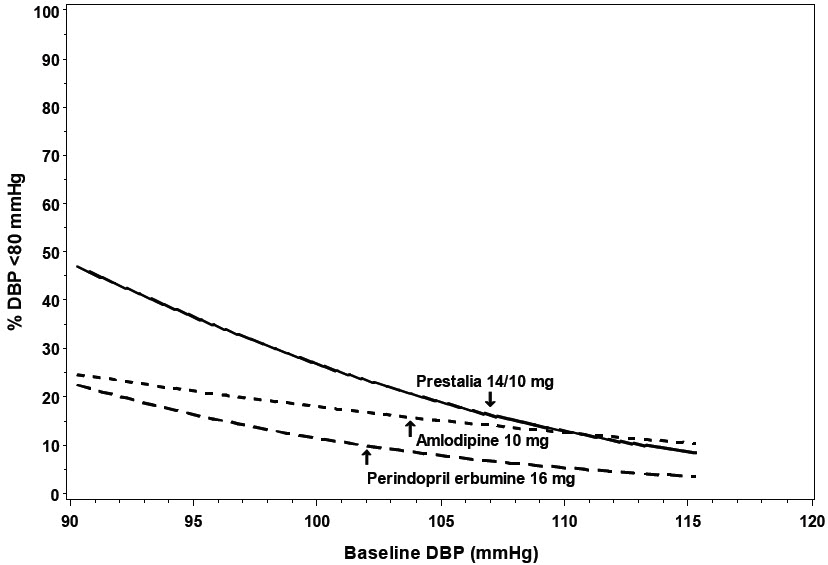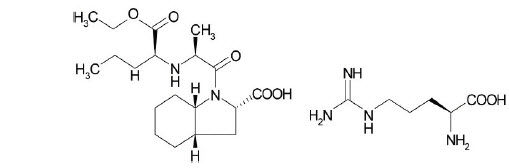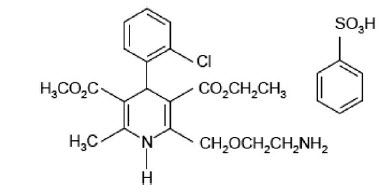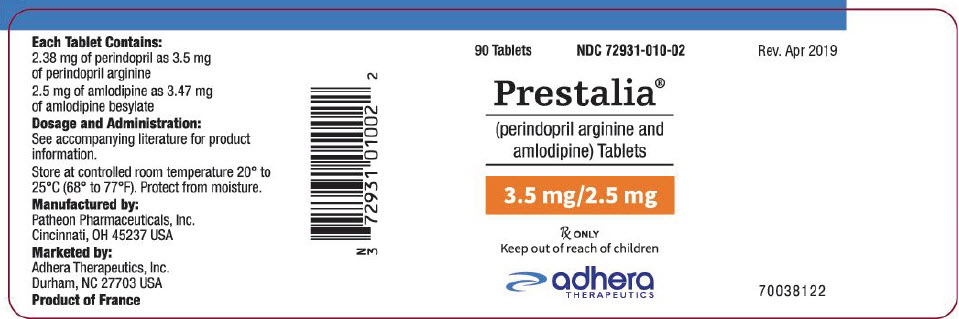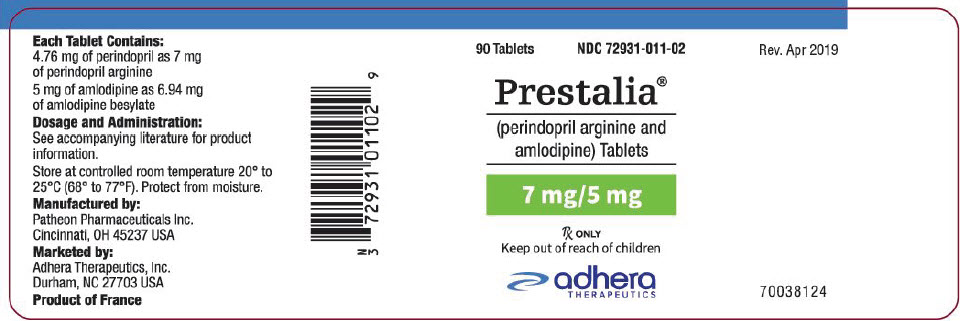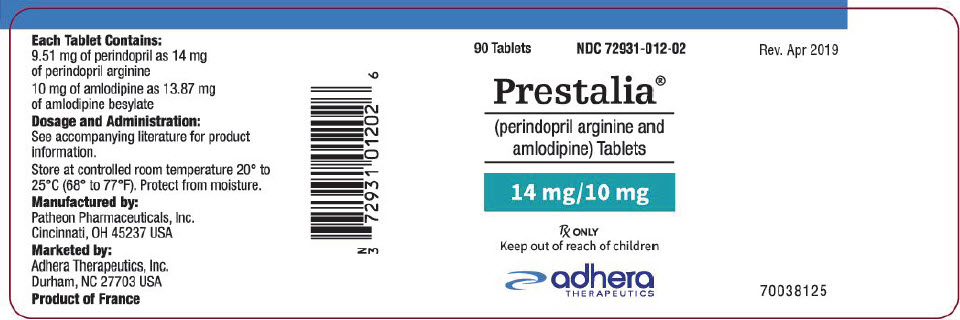 DRUG LABEL: Prestalia
NDC: 72931-010 | Form: TABLET
Manufacturer: Adhera Therapeutics, Inc.
Category: prescription | Type: HUMAN PRESCRIPTION DRUG LABEL
Date: 20191025

ACTIVE INGREDIENTS: perindopril arginine 3.5 mg/1 1; amlodipine besylate 2.5 mg/1 1
INACTIVE INGREDIENTS: lactose monohydrate; magnesium stearate; MICROCRYSTALLINE CELLULOSE; silicon dioxide

HIGHLIGHTS OF PRESCRIBING INFORMATION

These highlights do not include all the information needed to use PRESTALIA® tablets safely and effectively. See full prescribing information for PRESTALIA.
PRESTALIA (perindopril arginine and amlodipine) tablets, for oral use.
Initial U.S. Approval: 2015

WARNING: FETAL TOXICITY

See full prescribing information for complete boxed warning.

- When pregnancy is detected, discontinue PRESTALIA as soon as possible. (5.1)
- Drugs that act directly on the renin-angiotensin system can cause injury and death to the developing fetus. (5.1)

1 INDICATIONS AND USAGE

Prestalia is a combination of perindopril, an angiotensin converting enzyme inhibitor, and amlodipine, a dihydropyridine calcium channel blocker, indicated for the treatment of hypertension to lower blood pressure:

- In patients not adequately controlled with monotherapy (1).
- As initial therapy in patients likely to need multiple drugs to achieve their blood pressure goals (1).

Lowering blood pressure reduces the risk of fatal and nonfatal cardiovascular events, primarily strokes and myocardial infarctions (1).

2 DOSAGE AND ADMINISTRATION

- Initiate treatment at 3.5/2.5 mg, once daily. Adjust dose according to blood pressure goals waiting 1 to 2 weeks between titration steps (2.1).

3 DOSAGE FORMS AND STRENGTHS

- Tablets (perindopril arginine/amlodipine): 3.5/2.5 mg, 7/5 mg and 14/10 mg (3).

4 CONTRAINDICATIONS

- History of angioedema, or hypersensitivity to any ACE-inhibitor or to amlodipine (4).
- Do not use aliskiren with PRESTALIA in patients with diabetes (4).
- Do not take a neprilysin inhibitor with PRESTALIA (4).
- Do not administer PRESTALIA within 36 hours of switching to or from sacubitril/valsartan (4).

5 WARNINGS AND PRECAUTIONS

- Anaphylactoid reactions, including angioedema (head, neck, or intestinal) (5.2).
- Myocardial infarction: Worsening angina and acute myocardial infarction can develop after starting or increasing the dose of PRESTALIA, particularly in patients with severe obstructive coronary artery disease (5.3).
- Assess for hypotension and hyperkalemia (5.4, 5.5).
- Monitor renal function during therapy (5.7).

6 ADVERSE REACTIONS

The most common adverse reactions were edema (7.2%), cough (3.2%), headache (2.5%), and dizziness (2.5%) (6.1).

To report SUSPECTED ADVERSE REACTIONS, contact Adhera Therapeutics at 1-866-561-3088 or FDA at 1-800-FDA-1088 or www.fda.gov/medwatch.

7 DRUG INTERACTIONS

- Potassium supplements and potassium-sparing diuretics: risk of hyperkalemia (7).
- Lithium: increased serum lithium levels; toxicity symptoms (7).
- Injectable gold: flushing, nausea, vomiting, or hypotension (7).
- Dual inhibition of the renin-angiotensin system: increased risk of renal impairment, hypotension, and hyperkalemia (7).
- Do not exceed doses greater than 20 mg daily of simvastatin (7).
- NSAIDs: risk of renal impairment and loss of antihypertensive effect (7).
- Diuretics: increased risk of hypotension, consider dose reduction (7).
- CYP3A inhibitors: risk of hypotension and edema (7)
- Neprilysin Inhibitor: risk of angioedema (7).

8 USE IN SPECIFIC POPULATIONS

- Nursing Mothers: Discontinue nursing or PRESTALIA (8.3)
- Geriatrics: Monitor blood pressure for up to two weeks following titrations at doses above 7/5 mg in patients >65 years old.(8.5).
- Renal Impairment: Not recommended in patients with creatinine clearances <30 mL/min. For patients with mild or moderate impairment, do not exceed 7/5 mg (2.3, 5.7, 8.6).

FULL PRESCRIBING INFORMATION

WARNING: FETAL TOXICITY

- When pregnancy is detected, discontinue PRESTALIA as soon as possible [see Warnings and Precautions (5.1)].
- Drugs that act directly on the renin-angiotensin system can cause injury and death to the developing fetus [see Warnings and Precautions (5.1)].

1 INDICATIONS AND USAGE

PRESTALIA contains perindopril arginine, an angiotensin converting enzyme inhibitor, and amlodipine, a dihydropyridine calcium channel blocker, and is indicated for the treatment of hypertension, to lower blood pressure.

PRESTALIA may be used in patients whose blood pressure is not adequately controlled on monotherapy.

PRESTALIA may be used as initial therapy in patients likely to need multiple drugs to achieve blood pressure goals.

Lowering blood pressure reduces the risk of fatal and nonfatal cardiovascular events, primarily strokes and myocardial infarctions.

These benefits have been seen in controlled trials of antihypertensive drugs from a wide variety of pharmacologic classes, including amlodipine and the ACE inhibitor class to which perindopril principally belongs. There are no controlled trials demonstrating risk reduction with PRESTALIA.

Control of high blood pressure should be part of comprehensive cardiovascular risk management, including, as appropriate, lipid control, diabetes management, antithrombotic therapy, smoking cessation, exercise, and limited sodium intake. Many patients will require more than one drug to achieve blood pressure goals. For specific advice on goals and management, see published guidelines, such as those of the National High Blood Pressure Education Program's Joint National Committee on Prevention, Detection, Evaluation, and Treatment of High Blood Pressure (JNC).

Numerous antihypertensive drugs, from a variety of pharmacologic classes and with different mechanisms of action, have been shown in randomized controlled trials to reduce cardiovascular morbidity and mortality, and it can be concluded that it is blood pressure reduction, and not some other pharmacologic property of the drugs, that is largely responsible for those benefits. The largest and most consistent cardiovascular outcome benefit has been a reduction in the risk of stroke, but reductions in myocardial infarction and cardiovascular mortality also have been seen regularly.

Elevated systolic or diastolic pressure causes increased cardiovascular risk, and the absolute risk increase per mmHg is greater at higher blood pressures, so that even modest reductions of severe hypertension can provide substantial benefit. Relative risk reduction from blood pressure reduction is similar across populations with varying absolute risk, so the absolute benefit is greater in patients who are at higher risk independent of their hypertension (for example, patients with diabetes or hyperlipidemia), and such patients would be expected to benefit from more aggressive treatment to a lower blood pressure goal.

Some antihypertensive drugs have smaller blood pressure effects (as monotherapy) in black patients, and many antihypertensive drugs have additional approved indications and effects (e.g., on angina, heart failure, or diabetic kidney disease). These considerations may guide selection of therapy. In a clinical trial of PRESTALIA, treatment with PRESTALIA 14/10 mg did not provide additional antihypertensive effect beyond that achieved with use of amlodipine 10 mg in black and diabetic patients [see Clinical Studies (14)].

The choice of PRESTALIA as initial therapy for hypertension should be based on an assessment of potential benefits and risks including whether the patient is likely to tolerate the starting dose of PRESTALIA.

Patients with moderate-to-severe hypertension are at a relatively high risk of cardiovascular events (e.g., stroke, heart attack, and heart failure), kidney failure, and vision problems, so prompt treatment is clinically relevant. Consider the patient's baseline blood pressure, target goal and the incremental likelihood of achieving the goal with a combination product, such as PRESTALIA, versus a monotherapy product when deciding upon initial therapy. Individual blood pressure goals may vary based on the patient's risk.

Data from an 6-week, active-controlled trial provide estimates of the probability of reaching a target blood pressure with PRESTALIA compared with perindopril erbumine or amlodipine monotherapy [see Clinical Studies (14)].

Figures 1.a-1.d provide estimates of the likelihood of achieving target clinic systolic and diastolic blood pressure control with PRESTALIA 14/10 mg tablets after 6 weeks, based on baseline systolic and diastolic blood pressure. The curve for each treatment group was estimated by logistic regression modeling and is less well defined in the tails.

Figure 1.a Probability of Achieving Systolic Blood Pressure <140 mmHg at Week 6

Figure 1.b Probability of Achieving Systolic Blood Pressure <130 mmHg at Week 6

Figure 1.c Probability of Achieving Diastolic Blood Pressure <90 mmHg at Week 6

Figure 1.d Probability of Achieving Diastolic Blood Pressure <80 mmHg at Week 6

For example, a patient with a baseline blood pressure of 170/105 mmHg has approximately a 26% likelihood of achieving a goal of <140 mmHg (systolic) and 31% likelihood of achieving <90 mmHg (diastolic) on perindopril erbumine 16 mg. The likelihood of achieving these same goals on amlodipine 10 mg is approximately 40% (systolic) and 46% (diastolic). These likelihoods rise to 50% (systolic) and 65% (diastolic) with PRESTALIA 14/10 mg.

2 DOSAGE AND ADMINISTRATION

2.1 General Considerations

The recommended starting dose of PRESTALIA is 3.5/2.5 mg once daily.

Adjust dosage according to blood pressure goals. In general, wait 7 to 14 days between titration steps. The maximum recommended dose is 14/10 mg once daily [see Clinical Pharmacology (12.3)].

PRESTALIA may be used as initial therapy if a patient is likely to need multiple drugs to achieve blood pressure goals. Consider use in patients unable to achieve adequate antihypertensive effect with amlodipine monotherapy because of dose-limiting peripheral edema caused by amlodipine [see Adverse Reactions (6)].

Administered as monotherapy, perindopril erbumine is an effective treatment for hypertension in once-daily doses ranging from 4 mg to 16 mg daily. Amlodipine is effective in once-daily doses of 5 mg and 10 mg. Adverse reactions related to perindopril are generally uncommon and independent of dose, while those related to amlodipine are a mixture of dose-dependent phenomena (primarily peripheral edema) and dose-independent phenomena, the former much more common than the latter [see Adverse Reactions (6)].

2.2 Dosage Adjustment in Renal Impairment

PRESTALIA is not recommended in patients with creatinine clearances <30 mL/min. For patients with creatinine clearance between 30 and 80 mL/min (mild or moderate renal impairment), do not exceed 7/5 mg [see Use in Specific Populations (8.6) and Warnings and Precautions (5.7)].

2.3 Monitoring in Elderly Patients (Over 65 Years of Age)

Monitor blood pressure for up to two weeks following titrations at dosages above 7/5 mg in patients over 65 years of age [see Use in Specific Populations (8.5) and Clinical Pharmacology (12.3)].

3 DOSAGE FORMS AND STRENGTHS

PRESTALIA is available as fixed dose combination tablets of perindopril arginine and amlodipine:

- 3.5/2.5 mg tablets: white, uncoated tablets debossed with 3.5 on one side and 2.5 on the other side.
- 7/5 mg tablets: white, uncoated tablets debossed with 7/5 on one side and blank on the other side.
- 14/10 mg tablets: white, uncoated tablets debossed with 14/10 on one side and blank on the other side.

4 CONTRAINDICATIONS

PRESTALIA tablets are contraindicated in patients with hereditary or idiopathic angioedema, with or without previous ACE inhibitor treatment, and in patients who are hypersensitive to perindopril, to any other ACE inhibitor, or to amlodipine.

Do not co-administer aliskiren with ACE inhibitors, including PRESTALIA, in patients with diabetes.

Prestalia is contraindicated in combination with neprilysin inhibitor (e.g., sacubitril). Do not administer Prestalia within 36 hours of switching to or from sacubitril/valsartan, a neprilysin inhibitor [see Warnings and Precautions (5.2)].

5 WARNINGS AND PRECAUTIONS

5.1 Fetal Toxicity

Pregnancy Category D

Use of drugs that act on the renin-angiotensin system during the second and third trimesters of pregnancy reduces fetal renal function and increases fetal and neonatal morbidity and death. Resulting oligohydramnios can be associated with fetal lung hypoplasia and skeletal deformations. Potential neonatal adverse effects include skull hypoplasia, anuria, hypotension, renal failure, and death. When pregnancy is detected, discontinue PRESTALIA as soon as possible [see Use in Specific Populations (8.1)].

5.2 Anaphylactoid and Possibly Related Reactions

Angiotensin converting enzyme inhibitors affect the metabolism of eicosanoids and polypeptides, including endogenous bradykinin. Patients taking ACE inhibitors (including the one in PRESTALIA) may, therefore, be subject to a variety of bradykinin- or prostaglandin-mediated adverse reactions, some of them serious. Black patients receiving ACE inhibitors have a higher incidence of angioedema compared with non-blacks.

Head and Neck Angioedema: Angioedema of the face, extremities, lips, tongue, glottis, and larynx has been reported in patients treated with ACE inhibitors (0.1% of patients treated with perindopril in U.S. clinical trials). Angioedema associated with involvement of the tongue, glottis or larynx may be fatal. In such cases, discontinue perindopril treatment immediately and observe until the swelling disappears. When involvement of the tongue, glottis, or larynx appears likely to cause airway obstruction, administer appropriate therapy, such as subcutaneous epinephrine solution 1:1000 (0.3 to 0.5 mL), promptly.

Patients taking concomitant mTOR inhibitor (e.g. temsirolimus) therapy or a neprilysin inhibitor may be at increased risk for angioedema [see Drug Interactions (7)].

Intestinal Angioedema: Intestinal angioedema has been reported in patients treated with ACE inhibitors. These patients presented with abdominal pain (with or without nausea or vomiting), and the angioedema was diagnosed by imaging studies such as abdominal CT or ultrasound, or at surgery. In some cases there was no prior history of facial angioedema, and C-1 esterase levels were normal. Symptoms resolved after stopping the ACE inhibitor. Intestinal angioedema should be included in the differential diagnosis of patients on ACE inhibitors presenting with abdominal pain.

5.3 Increased Angina and/or Myocardial Infarction

Worsening angina and acute myocardial infarction can develop after starting or increasing the dose of PRESTALIA, particularly in patients with severe obstructive coronary artery disease.

5.4 Hypotension

PRESTALIA can cause symptomatic hypotension. Symptomatic hypotension is most likely to occur in patients who have been volume- or salt-depleted as a result of prolonged diuretic therapy, dietary salt restriction, dialysis, diarrhea, or vomiting.

In patients at risk of excessive hypotension, start PRESTALIA therapy under close medical supervision. Follow patients closely for the first 2 weeks of treatment and whenever the dose of PRESTALIA is increased or a diuretic is added or its dose increased.

If excessive hypotension occurs, immediately place patient in a supine position and, if necessary, treat patient with an intravenous infusion of physiological saline. PRESTALIA treatment can usually be continued following restoration of volume and blood pressure.

Patients with severe aortic stenosis may be more likely to experience symptomatic hypotension. Because of the gradual onset of action, acute hypotension is unlikely.

Surgery/Anesthesia

In patients undergoing major surgery or during anesthesia with agents that produce hypotension, PRESTALIA may block angiotensin II formation secondary to compensatory renin release. If hypotension occurs and is considered to be due to this mechanism, it can be corrected by volume expansion.

5.5 Hyperkalemia

Elevations of serum potassium have been observed in some patients treated with ACE inhibitors, including PRESTALIA. Risk factors for the development of hyperkalemia include renal insufficiency, diabetes mellitus, and the concomitant use of agents such as potassium-sparing diuretics, potassium supplements, and/or potassium-containing salt substitutes [see Drug Interactions (7)].

Monitor serum potassium periodically in patients receiving PRESTALIA.

5.6 Cough

Presumably because of the inhibition of the degradation of endogenous bradykinin, persistent nonproductive cough has been reported with all ACE inhibitors, generally resolving after discontinuation of therapy. Consider ACE inhibitor-induced cough in the differential diagnosis of cough.

5.7 Impaired Renal Function

Monitor renal function periodically in patients receiving PRESTALIA. Drugs that affect the renin-angiotensin system can cause reductions in renal function, including acute renal failure. Patients whose renal function may depend in part on the activity of the renin-angiotensin system—(e.g., patients with renal artery stenosis, severe heart failure, post-myocardial infarction or volume depletion) or who are on non-steroidal anti-inflammatory agents (NSAIDS) or angiotensin receptor blockers—may be at particular risk of developing acute renal failure on PRESTALIA. Consider withholding or discontinuing therapy in patients who develop a clinically significant decrease in renal function on PRESTALIA.

5.8 Hepatic Failure

Rarely, ACE inhibitors have been associated with a syndrome that starts with cholestatic jaundice and progresses to fulminant hepatic necrosis and sometimes death. The mechanism of this syndrome is not understood. Patients receiving ACE inhibitors who develop jaundice or marked elevations of hepatic enzymes should discontinue the ACE inhibitor and receive appropriate medical follow-up.

6 ADVERSE REACTIONS

6.1 Clinical Trials Experience

Because clinical trials are conducted under widely varying conditions, adverse reaction rates observed in the clinical trials of a drug cannot be directly compared to rates in the clinical trials of another drug and may not reflect the rates observed in practice.

In an active-controlled 6-week trial, the safety of the maximum dose of PRESTALIA (14/10 mg) was evaluated in 279 patients with hypertension and compared with perindopril erbumine 16 mg and amlodipine 10 mg. Adverse reactions were generally mild and transient in nature.

Discontinuations because of adverse events occurred in 3.6% of patients treated with PRESTALIA 14/10 mg compared to 4.3% of patients treated with perindopril erbumine 16 mg and 4.6% of patients treated with amlodipine 10 mg. The most common reason for discontinuation of therapy with PRESTALIA was peripheral edema (1.8%).

Common adverse events that occurred in at least 2% of patients treated with PRESTALIA in the 6-week trial are presented in Table 1.

Table 1: Adverse Reactions Occurring at an Incidence of ≥2% in PRESTALIA-Treated Patients
Adverse Event | PRESTALIA 14/10 mg (N = 279) n (%) | PERe 16 mg (N = 278) n (%) | AML 10 mg (N = 280) n (%)
Edema peripheral | 20 (7.2) | 1 (0.4) | 37 (13.2)
Cough | 9 (3.2) | 8 (2.9) | 2 (0.7)
Headache | 7 (2.5) | 8 (2.9) | 8 (2.9)
Dizziness | 7 (2.5) | 4 (1.4) | 3 (1.1)
PERe = perindopril erbumine; AML = amlodipine besylate

The overall frequency of adverse reactions was similar between men and women, and black and non-black patients. In black patients, the incidence of peripheral edema was similar in the PRESTALIA 14/10 mg and amlodipine 10 mg arms (3%).

Other adverse reactions in the controlled clinical trial with some plausible relationship to PRESTALIA are listed below.

Dermatologic: Rash

Digestive: Nausea, diarrhea

The safety of the lowest dose of PRESTALIA (3.5/2.5 mg) was evaluated in 249 patients with hypertension and compared with placebo and perindopril and amlodipine administered as monotherapies in an 8-week trial. The only emergent adverse event observed in at least 2% of patients treated with PRESTALIA was hyperkalemia (2.4%). Peripheral edema was reported in 1.6% of patients receiving PRESTALIA 3.5/2.5 mg.

Monotherapy with perindopril or amlodipine has been evaluated for safety in clinical trials in over 3,000 and 11,000 patients, respectively, as summarized below.

Perindopril

Perindopril erbumine has been evaluated for safety in approximately 3,400 patients with hypertension in U.S. and foreign clinical trials. The data presented here are based on results from the 1,417 perindopril-treated patients who participated in the U.S. clinical trials. Over 220 of these patients were treated with perindopril for at least one year.

In placebo-controlled U.S. clinical trials, the incidence of premature discontinuation of therapy due to adverse events was 6.5% in patients treated with perindopril erbumine and 6.7% in patients treated with placebo. The most common causes were cough, headache, asthenia, and dizziness.

Among 1,012 patients in placebo-controlled U.S. trials, the overall frequency of reported adverse events was similar in patients treated with perindopril erbumine and in those treated with placebo (approximately 75% in each group). The only adverse events whose incidence on perindopril erbumine was at least 2% greater than on placebo were cough (12% vs. 4.5%) and back pain (5.8% vs. 3.1%).

Dizziness was not reported more frequently in the perindopril group (8.2%) than in the placebo group (8.5%), but its likelihood increased with dose, suggesting a causal relationship with perindopril.

Amlodipine

Amlodipine has been evaluated for safety in more than 11,000 patients in U.S. and foreign clinical trials. In controlled clinical trials comparing amlodipine (N=1730) in doses up to 10 mg with placebo (N=1250), discontinuation of amlodipine due to adverse reactions was required in about 1.5% of amlodipine-treated patients and about 1% of placebo-treated patients. The most common side effects were edema, dizziness, flushing, and palpitations.

The following events occurred in <1% but >0.1% of patients in controlled clinical trials or under conditions of open trials or marketing experience where a causal relationship is uncertain; they are listed to alert the physician to a possible relationship:

Cardiovascular: arrhythmia (including ventricular tachycardia and atrial fibrillation), bradycardia, chest pain, peripheral ischemia, syncope, tachycardia, vasculitis.

Central and Peripheral Nervous System: hypoesthesia, neuropathy peripheral, paresthesia, tremor, vertigo.

Gastrointestinal: anorexia, constipation, dysphagia, diarrhea, flatulence, pancreatitis, vomiting, gingival hyperplasia.

General: allergic reaction, asthenia, [These events occurred in less than 1% in placebo-controlled trials, but the incidence of these side effects was between 1% and 2% in all multiple dose studies.] back pain, hot flushes, malaise, pain, rigors, weight gain, weight decrease.

Musculoskeletal System: arthralgia, arthrosis, muscle cramps, myalgia.

Psychiatric: sexual dysfunction (male and female), insomnia, nervousness, depression, abnormal dreams, anxiety, depersonalization.

Respiratory System: dyspnea, epistaxis.

Skin and Appendages: angioedema, erythema multiforme, pruritus, rash, rash erythematous, rash maculopapular.

Special Senses: abnormal vision, conjunctivitis, diplopia, eye pain, tinnitus.

Urinary System: micturition frequency, micturition disorder, nocturia.

Autonomic Nervous System: dry mouth, sweating increased.

Metabolic and Nutritional: hyperglycemia, thirst.

Hematopoietic: leukopenia, purpura, thrombocytopenia.

Clinical Laboratory Findings

Perindopril

Hematology: Small decreases in hemoglobin and hematocrit occur frequently in hypertensive patients treated with perindopril, but are rarely of clinical importance. In controlled clinical trials, no patient was discontinued from therapy due to the development of anemia. Leukopenia (including neutropenia) was observed in 0.1% of patients in U.S. clinical trials.

Liver Function Tests: Elevations in alanine transaminase (ALT; 1.6% perindopril erbumine vs. 0.9% placebo) and aspartate transaminase (AST; 0.5% perindopril erbumine vs. 0.4% placebo) have been observed in placebo-controlled clinical trials. The elevations were generally mild and transient and resolved after discontinuation of therapy.

6.2 Postmarketing Experience

The following adverse reactions have been identified during post-approval use of the individual components of PRESTALIA. Because these reactions are reported voluntarily from a population of uncertain size, it is not always possible to reliably estimate their frequency or establish a causal relationship to drug exposure.

Perindopril: Voluntary reports of adverse events in patients taking perindopril that have been received since market introduction and are of unknown causal relationship to perindopril include: cardiac arrest, eosinophilic pneumonitis, neutropenia/agranulocytosis, pancytopenia, anemia (including hemolytic and aplastic), thrombocytopenia, acute renal failure, nephritis, hepatic failure, jaundice (hepatocellular or cholestatic), symptomatic hyponatremia, bullous pemphigoid, pemphigus, acute pancreatitis, falls, psoriasis, exfoliative dermatitis, and a syndrome that may include: arthralgia/arthritis, vasculitis, serositis, myalgia, fever, rash or other dermatologic manifestations, a positive antinuclear antibody (ANA), leukocytosis, eosinophilia, or an elevated erythrocyte sedimentation rate (ESR).

Amlodipine: The following postmarketing event has been reported infrequently where a causal relationship is uncertain: palpitations, gynecomastia, jaundice and hepatic enzyme elevations (mostly consistent with cholestasis or hepatitis), some requiring hospitalization.

7 DRUG INTERACTIONS

Prestalia

The pharmacokinetics of perindopril and amlodipine are not altered when the drugs are co-administered.

No drug interaction studies have been conducted with PRESTALIA, although studies have been conducted with perindopril and amlodipine.

mTOR Inhibitors: Patients taking concomitant mTOR inhibitor (e.g. temsirolimus) therapy may be at increased risk for angioedema. [see Warnings and Precautions (5.2)]

Neprilysin Inhibitor: Patients taking concomitant neprilysin inhibitors may be at increased risk for angioedema. [see Warnings and Precautions (5.2)].

Perindopril

Diuretics: Patients on diuretics, especially those in whom diuretic therapy was recently instituted, may occasionally experience an excessive reduction of blood pressure after initiation of therapy with PRESTALIA. Provide close medical supervision with the first dose of PRESTALIA, for at least two hours and until blood pressure has stabilized for another hour. Perindopril can attenuate potassium loss caused by thiazide diuretics.

Potassium Supplements and Potassium-Sparing Diuretics: Potassium-sparing diuretics (spironolactone, amiloride, triamterene, and others) or potassium supplements, or other drugs capable of increasing serum potassium (indomethacin, heparin, cyclosporine and others) can increase the risk of hyperkalemia. If concomitant use of such agents is indicated, the patient's serum potassium should be monitored frequently.

Lithium: Increased serum lithium levels and symptoms of lithium toxicity have been reported in patients receiving ACE inhibitors during therapy with lithium. When co-administering PRESTALIA and lithium, frequent monitoring of serum lithium levels is recommended. Use of a diuretic may further increase the risk of lithium toxicity.

Gold: Nitritoid reactions (symptoms include facial flushing, nausea, vomiting, and hypotension) have been reported rarely in patients on therapy with injectable gold (sodium aurothiomalate) and concomitant ACE inhibitor therapy.

Non-Steroidal Anti-Inflammatory Agents (NSAIDS) Including Selective Cyclooxygenase-2 Inhibitors (COX-2 Inhibitors): In patients who are elderly, volume-depleted (including those on diuretic therapy), or with compromised renal function, co-administration of NSAIDS, including selective COX-2 inhibitors, with ACE inhibitors, including perindopril, may result in deterioration of renal function, including possible acute renal failure. These effects are usually reversible. Monitor renal function periodically in patients receiving perindopril and NSAID therapy.

The antihypertensive effects of ACE inhibitors, including perindopril, may be attenuated by NSAIDS, including selective COX-2 inhibitors.

Dual Blockade of the Renin-Angiotensin System (RAS): Dual blockade of the RAS with angiotensin receptor blockers, ACE inhibitors, or aliskiren is associated with increased risks of hypotension, hyperkalemia, and changes in renal function (including acute renal failure) compared to monotherapy. In most patients no benefit has been associated with using two RAS inhibitors concomitantly. In general, avoid combined use of RAS inhibitors. Closely monitor blood pressure, renal function, and electrolytes in patients on PRESTALIA and other agents that affect the RAS.

Do not co-administer aliskiren with PRESTALIA in patients with diabetes. Avoid use of aliskiren with PRESTALIA in patients with renal impairment (GFR <60 mL/min).

Amlodipine

Simvastatin: Co-administration of multiple doses of 10 mg of amlodipine with 80 mg simvastatin resulted in a 77% increase in exposure to simvastatin compared to simvastatin administered alone. Limit the dose of simvastatin in patients on amlodipine to 20 mg daily.

Cyclosporine: A prospective study in renal transplant patients showed an average 40% increase in trough levels during concomitant treatment with amlodipine. Frequent monitoring of trough blood levels of cyclosporine is recommended.

CYP3A Inhibitors: Co-administration of the moderate CYP3A inhibitor diltiazem increases the exposure to amlodipine by 60%. Co-administered erythromycin, also a moderate CYP3A inhibitor, does not impact the exposure to amlodipine. Strong CYP3A inhibitors (e.g., itraconazole) may increase the plasma concentrations of the CYP3A substrate amlodipine to a greater extent. Monitor for symptoms of hypotension and edema when amlodipine is co-administered with moderate or strong CYP3A inhibitors to determine the need for dose adjustment.

CYP3A Inducers: No information is available on the quantitative effects of CYP3A inducers on amlodipine. Blood pressure should be monitored when amlodipine is co-administered with CYP3A inducers.

8 USE IN SPECIFIC POPULATIONS

8.1 Pregnancy

TERATOGENIC EFFECTS

Pregnancy Category D [see Warnings and Precautions (5.1)]

Use of drugs that act on the renin-angiotensin system during the second and third trimesters of pregnancy reduces fetal renal function and increases fetal and neonatal morbidity and death. Resulting oligohydramnios can be associated with fetal lung hypoplasia and skeletal deformations. Potential neonatal adverse effects include skull hypoplasia, anuria, hypotension, renal failure, and death. When pregnancy is detected, discontinue PRESTALIA as soon as possible. These adverse outcomes are usually associated with use of these drugs in the second and third trimester of pregnancy. Most epidemiologic studies examining fetal abnormalities after exposure to antihypertensive use in the first trimester have not distinguished drugs affecting the renin-angiotensin system from other antihypertensive agents. Appropriate management of maternal hypertension during pregnancy is important to optimize outcomes for both mother and fetus.

In the unusual case that there is no appropriate alternative therapy with drugs affecting the renin-angiotensin system for a particular patient, apprise the mother of the potential risk to the fetus. Perform serial ultra-sound examinations to assess the intra-amniotic environment. If oligohydramnios is observed, discontinue PRESTALIA, unless it is considered lifesaving for the mother. Fetal testing may be appropriate, based on the week of pregnancy. Patients and physicians should be aware, however, that oligohydramnios may not appear until after the fetus has sustained irreversible injury. Closely observe infants with histories of in utero exposure to PRESTALIA for hypotension, oliguria, and hyperkalemia [see Use in Specific Populations (8.4)].

Radioactivity was detectable in fetuses after administration of ^14C-perindopril to pregnant rats.

8.3 Nursing Mothers

It is not known whether perindopril or amlodipine is excreted in human milk, but radioactivity was detected in the milk of lactating rats following administration of ^14C-perindopril. Because of the potential for adverse effects on the nursing infant, decide whether to discontinue nursing or discontinue PRESTALIA.

8.4 Pediatric Use

Neonates with a history of in utero exposure to PRESTALIA:

If oliguria or hypotension occurs, direct attention toward support of blood pressure and renal perfusion. Exchange transfusions or dialysis may be required as a means of reversing hypotension and/or substituting for disordered renal function.

The safety and effectiveness of PRESTALIA in pediatric patients have not been established.

8.5 Geriatric Use

The mean blood pressure effect of perindopril was somewhat smaller in patients over 60 years of age than in younger patients, although the difference was not significant. Plasma concentrations of both perindopril and perindoprilat in elderly patients (>65 years) are approximately twice those observed in younger patients. No adverse effects were clearly increased in older patients with the exception of dizziness and rash.

Amlodipine is extensively metabolized in the liver. In the elderly, clearance of amlodipine is decreased with resulting increases in peak plasma levels, elimination half-life, and AUC.

Experience with PRESTALIA is limited in the elderly at doses exceeding 7/5 mg. If doses above 7/5 mg are required, monitor blood pressure up to two weeks following up titration [see Dosage and Administration (2.2) and Clinical Pharmacology (12.3)].

8.6 Renal Impairment

Pharmacokinetic data indicate that perindoprilat elimination is decreased in renally impaired patients, with a marked increase in accumulation when creatinine clearance drops below 30 mL/min. PRESTALIA is not recommended in patients with creatinine clearances <30 mL/min. For patients with creatinine clearance between 30 and 80 mL/min (mild or moderate renal impairment), do not exceed 7/5 mg [see Dosage and Administration (2.2) and Clinical Pharmacology (12.3)].

10 OVERDOSAGE

Perindopril

In animals, doses of perindopril up to 2,500 mg/kg in mice, 3,000 mg/kg in rats and 1,600 mg/kg in dogs were non-lethal. Past experiences were scant but suggested that overdosage with other ACE inhibitors was also fairly well tolerated by humans. The most likely manifestation is hypotension, and treatment should be symptomatic and supportive. Therapy with the ACE inhibitor should be discontinued, and the patient should be observed. Dehydration, electrolyte imbalance and hypotension should be treated by established procedures.

Among the reported cases of perindopril overdosage, patients who were known to have ingested a dose of 80 mg to 120 mg required assisted ventilation and circulatory support. One additional patient developed hypothermia, circulatory arrest and died following ingestion of up to 180 mg of perindopril. The intervention for perindopril overdose may require vigorous support.

Laboratory determinations of serum levels of perindopril and its metabolites are not widely available, and such determinations have, in any event, no established role in the management of perindopril overdose. No data are available to suggest physiological maneuvers (e.g., maneuvers to change the pH of the urine) that might accelerate elimination of perindopril and its metabolites.

Angiotensin II could presumably serve as a specific antagonist-antidote in the settling of perindopril overdose, but angiotensin II is essentially unavailable outside of scattered research facilities. Because the hypotensive effect of perindopril is achieved through vasodilation and effective hypovolemia, it is reasonable to treat perindopril overdose by infusion of normal saline solution.

Amlodipine

Overdosage might be expected to cause excessive peripheral vasodilation with marked hypotension and possibly a reflex tachycardia. In humans, experience with intentional overdosage of amlodipine is limited.

Single oral doses of amlodipine maleate equivalent to 40 mg amlodipine/kg and 100 mg amlodipine/kg in mice and rats, respectively, caused deaths. Single oral amlodipine maleate doses equivalent to 4 or more mg amlodipine/kg or higher in dogs (11 or more times the maximum recommended human dose on a mg/m^2 basis) caused a marked peripheral vasodilation and hypotension.

If massive overdose should occur, initiate active cardiac and respiratory monitoring. Frequent blood pressure measurements are essential. Should hypotension occur, provide cardiovascular support including elevation of the extremities and the judicious administration of fluids. If hypotension remains unresponsive to these conservative measures, consider administration of vasopressors (such as phenylephrine) with attention to circulating volume and urine output. As amlodipine is highly protein bound, hemodialysis is not likely to be of benefit.

11 DESCRIPTION

PRESTALIA is a combination of perindopril arginine and amlodipine besylate.

Perindopril arginine is the L-arginine salt of perindopril, the ethyl ester of a non-sulfhydryl angiotensin converting enzyme inhibitor. Perindopril arginine is chemically described as L-arginine (2S,3aS,7aS)-1-[(2S)-2-[[(1S)-1-(ethoxycarbonyl)butyl]amino]propanoyl] octahydro-1H-indole-2-carboxylate. Its empirical formula is C19H32N2O5∙C6H14N4O2 and its structural formula is:

Perindopril arginine is a white, crystalline powder with a molecular weight 542.7. The free acid has the molecular weight of 368.5. It is readily soluble in purified water, slightly soluble in 95% ethanol, and practically insoluble in chloroform.

Perindopril is the free-acid form of perindopril arginine. Perindopril is a pro-drug and is metabolized in vivo by hydrolysis of the ester group to form perindoprilat, the biologically active metabolite.

Amlodipine besylate is the benzene sulphonic acid salt of amlodipine, a long-acting dihydropyridine calcium channel blocker. Amlodipine besylate is chemically described as 3-ethyl-5-methyl (±)-2-[(2-aminoethoxy)methyl]-4-(2-chlorophenyl)-1,4-dihydro-6-methyl-3,5-pyridinedicarboxylate monobenzenesulphonate. Its empirical formula is C20H25ClN2O5∙C6H6O3S and its structural formula is:

Amlodipine besylate is a white crystalline powder with a molecular weight of 567.1. It is slightly soluble in water and sparingly soluble in ethanol. The content of the tablets is expressed as amlodipine (free base) which has a molecular weight of 409.1.

PRESTALIA tablets are formulated in three different strengths for oral administration. Tablets contain perindopril arginine 3.5 mg, 7 mg, or 14 mg and amlodipine 2.5 mg, 5 mg, or 10 mg for the following available perindopril arginine/amlodipine combinations: 3.5/2.5 mg, 7/5 mg, and 14/10 mg.

Inactive ingredients are lactose, microcrystalline cellulose, colloidal silicon dioxide, and magnesium stearate.

12 CLINICAL PHARMACOLOGY

12.1 Mechanism of Action

Perindopril

Perindopril, a pro-drug, is hydrolyzed to perindoprilat, which inhibits ACE in humans and in animals. ACE is a peptidyl dipeptidase that catalyzes the conversion of the inactive decapeptide, angiotensin I, to the vasoconstrictor substance angiotensin II. Angiotensin II is a potent peripheral vasoconstrictor, which stimulates aldosterone secretion by the adrenal cortex, and provides negative feedback on renin secretion. Inhibition of ACE results in decreased plasma angiotensin II, leading to decreased vasoconstriction, increased plasma renin activity and decreased aldosterone secretion. The latter results in diuresis and natriuresis and may be associated with an increase in serum potassium [see Warnings and Precautions (5.6)].

ACE is identical to kininase II, an enzyme that degrades bradykinin. Whether increased levels of bradykinin, a potent vasodepressor peptide, play a role in the therapeutic effects of perindopril remains to be elucidated.

While the principal mechanism of perindopril in blood pressure reduction is believed to be through the renin-angiotensin-aldosterone system, ACE inhibitors have some effect even in apparent low-renin hypertension. Perindopril has been studied in relatively few black patients, usually a low-renin population, and the average response of diastolic blood pressure to perindopril was about half the response seen in nonblack patients, a finding consistent with previous experience of other ACE inhibitors.

Amlodipine

Amlodipine is a dihydropyridine calcium antagonist (calcium ion antagonist or slow channel blocker) that inhibits the transmembrane influx of calcium ions into vascular smooth muscle and cardiac muscle. Experimental data suggest that amlodipine binds to both dihydropyridine and nondihydropyridine binding sites. The contractile processes of cardiac muscle and vascular smooth muscle are dependent upon the movement of extracellular calcium ions into these cells through specific ion channels. Amlodipine inhibits calcium ion influx across cell membranes selectively, with a greater effect on vascular smooth muscle cells than on cardiac muscle cells. Negative inotropic effects can be detected in vitro but such effects have not been seen in intact animals at therapeutic doses.

Serum calcium concentration is not affected by amlodipine. Within the physiologic pH range, amlodipine is an ionized compound (pKa=8.6), and its kinetic interaction with the calcium channel receptor is characterized by a gradual rate of association and dissociation with the receptor binding site, resulting in a gradual onset of effect.

Amlodipine is a peripheral arterial vasodilator that acts directly on vascular smooth muscle to cause a reduction in peripheral vascular resistance and reduction in blood pressure.

12.2 Pharmacodynamics

Perindopril

After administration of perindopril, ACE is inhibited in a dose and blood concentration-related fashion. The degree of ACE inhibition achieved by a given dose appears to diminish over time (the ID50 increases). The pressor response to an angiotensin I infusion is reduced by perindopril, but this is not as persistent as the effect on ACE.

Amlodipine

Following administration of therapeutic doses to patients with hypertension, amlodipine produces vasodilation resulting in a reduction of supine and standing blood pressures. These decreases in blood pressure are not accompanied by a significant change in heart rate or plasma catecholamine levels with chronic dosing. Although the acute intravenous administration of amlodipine decreases arterial blood pressure and increases heart rate in hemodynamic studies of patients with chronic stable angina, chronic oral administration of amlodipine in clinical trials did not lead to clinically significant changes in heart rate or blood pressures in normotensive patients with angina.

With chronic once daily oral administration, antihypertensive effectiveness is maintained for at least 24 hours. Plasma concentrations correlate with effect in both young and elderly patients. The magnitude of reduction in blood pressure with amlodipine is also correlated with the height of pretreatment elevation; thus, individuals with moderate hypertension (diastolic pressure 105-114 mmHg) had about a 50% greater response than did patients with mild hypertension (diastolic pressure 90-104 mmHg). Normotensive subjects experienced no clinically significant change in blood pressures (+1/-2 mmHg).

In hypertensive patients with normal renal function, therapeutic doses of amlodipine resulted in a decrease in renal vascular resistance and an increase in glomerular filtration rate and effective renal plasma flow without change in filtration fraction or proteinuria.

As with other calcium channel blockers, hemodynamic measurements of cardiac function at rest and during exercise (or pacing) in patients with normal ventricular function treated with amlodipine have generally demonstrated a small increase in cardiac index without significant influence on dP/dt or on left ventricular end diastolic pressure or volume. In hemodynamic studies, amlodipine has not been associated with a negative inotropic effect when administered in the therapeutic dose range to intact animals and humans, even when co-administered with β-blockers to humans. Similar findings, however, have been observed in normal or well-compensated patients with heart failure with agents possessing significant negative inotropic effects.

Electrophysiologic Effects: Amlodipine does not change sinoatrial (SA) nodal function or atrioventricular (AV) conduction in intact animals or humans. In clinical studies in which amlodipine was administered in combination with β-blockers to patients with either hypertension or angina, no adverse effects on electrocardiographic parameters were observed.

12.3 Pharmacokinetics

Prestalia

Following administration of PRESTALIA, peak plasma concentration of perindopril, perindoprilat and amlodipine occur at approximately 1 hour, 4 hours and 6-12 hours, respectively. The mean half-life of perindopril is approximately 1.3 hours. The decline in the plasma concentration of perindoprilat is multiphasic and shows a terminal elimination half-life of approximately 100 hours, resulting from slow dissociation of perindoprilat from plasma/tissue ACE binding sites. Amlodipine elimination from plasma is biphasic with a terminal elimination half-life of approximately 30 to 50 hours.

When PRESTALIA is administered with food, the exposure to perindopril, perindoprilat and amlodipine is not impacted.

Perindopril

Following administration of PRESTALIA, perindopril is rapidly absorbed, with peak plasma concentrations occurring at approximately 1 hour. The absolute oral bioavailability of perindopril is approximately 75%. Following absorption, approximately 30% to 50% of systemically available perindopril is hydrolyzed to its active metabolite, perindoprilat, which has a mean bioavailability of approximately 25%. Peak plasma concentrations of perindoprilat are attained approximately 4 hours after PRESTALIA administration. Food had no effect on the extent of absorption of perindopril or perindoprilat, but slightly reduced the rate of absorption of perindopril and perindoprilat by 18% and 14%, respectively.

The Cmax and AUC of perindopril and perindoprilat increase in a linear and dose proportional manner following both single oral dosing and at steady state during an once-a-day multiple dosing regimen. Perindopril exhibits multiexponential pharmacokinetics following oral administration. The mean half-life of perindopril associated with most of its elimination is approximately 0.8 to 1 hours.

Perindopril is extensively metabolized following oral administration, with only 4% to 12% of the dose recovered unchanged in the urine. Six metabolites resulting from hydrolysis, glucuronidation, and cyclization via dehydration have been identified. These include the active ACE inhibitor perindoprilat (hydrolyzed perindopril), perindopril, and perindoprilat glucuronides, dehydrated perindopril, and the diastereoisomers of dehydrated perindoprilat. In humans, hepatic esterase appears to be responsible for the hydrolysis of perindopril.

The active metabolite, perindoprilat, also exhibits multiexponential pharmacokinetics following the oral administration of perindopril. Formation of perindoprilat is gradual with peak plasma concentrations occurring between 3 and 7 hours. The subsequent decline in plasma concentration shows a prolonged terminal elimination half-life of 120 hours resulting from slow dissociation of perindoprilat from plasma/tissue ACE binding sites. During repeated oral once-daily dosing with perindopril, perindoprilat accumulates about 1.5- to 2-fold and attains steady state plasma levels in 3 to 6 days. The clearance of perindoprilat and its metabolites is almost exclusively renal.

Approximately 60% of circulating perindopril is bound to plasma proteins, and only 10% to 20% of perindoprilat is bound. Therefore, drug interactions mediated through effects on protein binding are not anticipated.

Amlodipine

Absolute bioavailability of amlodipine has been estimated between 64% and 90%. Ex vivo studies indicate that approximately 93% of circulating amlodipine is bound to plasma proteins in hypertensive patients.

Amlodipine is extensively (approximately 90%) metabolized in the liver to inactive metabolites. Steady-state plasma levels are reached after once-daily dosing for 7 to 8 days. 10% of unchanged drug and 60% of amlodipine metabolites are excreted in urine.

Drug Interactions:

Perindopril: Co-administered perindopril does not impact the exposure to amlodipine or digoxin.

Amlodipine: Co-administered cimetidine, magnesium- and aluminum hydroxide antacids, sildenalfil, and grapefruit juice have no impact on the exposure to amlodipine. Co-administered amlodipine does not affect the exposure to perindopril, perindoprilat, atorvastatin, ethanol and the warfarin prothrombin response time.

Specific Populations

Elderly:

Perindopril: Plasma concentrations of both perindopril and perindoprilat in elderly patients (>65 years) are approximately twice those observed in younger patients, reflecting both increased conversion of perindopril to perindoprilat and decreased renal excretion of perindoprilat [see Dosing and Administration (2.2)and Use in Specific Populations (8.5)].

Amlodipine: Clearance of amlodipine is decreased in elderly patients, resulting in an increased area under the plasma concentration curve (AUC) of approximately 40% to 60% [see Dosing and Administration (2.3) and Use in Specific Populations (8.5)].

Renal Impairment:

Perindopril: Perindoprilat elimination is decreased in renally impaired patients. At creatinine clearances of 30 mL/min to 80 mL/min, AUC is about double that at 100 mL/min. When creatinine clearance drops below 30 mL/min, AUC increases more markedly [see Dosing and Administration (2.2) and Warnings and Precautions (5.7)].

During dialysis, perindopril is removed with the same clearance as in patients with normal renal function. In a limited number of patients studied, perindopril clearance by dialysis ranged from about 40 to 80 mL/min. Perindoprilat clearance by dialysis ranged from about 40 to 90 mL/min [see Dosing and Administration (2.2)].

Amlodipine: The pharmacokinetics of amlodipine is not significantly influenced by renal impairment [see Dosing and Administration (2.2) and Use in Specific Populations (8.6)].

Hepatic Impairment:

Perindopril: The bioavailability of perindoprilat is increased in patients with impaired hepatic function. Plasma concentrations of perindoprilat in patients with impaired liver function were about 50% higher than those observed in healthy subjects or hypertensive patients with normal liver function [see Warnings and Precautions (5.8)].

Amlodipine: Patients with hepatic insufficiency have decreased clearance of amlodipine with a resulting increase in AUC of approximately 40–60%.

Heart Failure:

Perindopril: Perindoprilat clearance is reduced in congestive heart failure patients, resulting in a 40% higher dose interval AUC.

Amlodipine: Patients with hepatic insufficiency have decreased clearance of amlodipine with a resulting increase in AUC of approximately 40–60%.

13 NONCLINICAL TOXICOLOGY

13.1 Carcinogenesis, Mutagenesis, Impairment of Fertility

No carcinogenicity, mutagenicity or fertility studies have been conducted with the combination of perindopril and amlodipine. However, these studies have been conducted for perindopril and amlodipine alone.

Perindopril

Carcinogenicity: No evidence of carcinogenicity was observed in studies in rats and mice when perindopril was administered at dosages up to 5 times (mg/m^2) the maximum recommended human dose (MRHD) of 14 mg/day for 104 weeks.

Mutagenesis: No genotoxic potential was detected for perindopril, perindoprilat, and other metabolites in various in vitro and in vivo investigations, including the Ames test, the Saccharomyces cerevisiae D4 test, cultured human lymphocytes, thymidine kinase ± mouse lymphoma assay, mouse and rat micronucleus tests, the in vivo micronucleus and chromosomal aberration tests, and Chinese hamster bone marrow assay.

Impairment of Fertility: There was no meaningful effect on reproductive performance or fertility in rats given up to 7 times (mg/m^2) the MRHD during the period of spermatogenesis in males or oogenesis and gestation in females.

Amlodipine

Carcinogenicity: Rats and mice treated with amlodipine maleate in the diet for up to 2 years, at concentrations calculated to provide daily amlodipine dosage levels of 0.5, 1.25, and 2.5 mg/kg/day, showed no evidence of a carcinogenic effect of the drug. For the mouse, the highest dose was, on a body surface area basis, similar to the amlodipine MRHD of 10 mg/day. For the rat, the highest dose was, on a body surface area basis, approximately 2.5 times the MRHD, assuming a patient weight of 60 kg.

Mutagenesis: Mutagenicity studies conducted with amlodipine maleate revealed no drug-related effects at either the gene or chromosome level.

Impairment of Fertility: There was no effect on the fertility of rats treated orally with amlodipine maleate (males for 64 days and females for 14 days prior to mating) at amlodipine doses of up to 10 mg/kg/day, about 10 times the MRHD of 10 mg/day on a body surface area basis.

13.3 Reproductive Toxicity

Reproductive toxicity studies have not been conducted with this combination. However, these studies have been conducted for amlodipine alone.

Amlodipine

No evidence of teratogenicity or other embryo/fetal toxicity was found when pregnant rats and rabbits were treated orally with amlodipine maleate at amlodipine doses of up to 10 mg/kg/day (respectively, about 8 and 23 times the maximum recommended human dose of 10 mg on a mg/m^2 basis, assuming a patient weight of 50 kg) during their periods of major organogenesis. However, litter size was significantly decreased (by about 50%) and the number of intrauterine deaths was significantly increased (about 5-fold) for rats receiving amlodipine maleate at an amlodipine dose equivalent to 10 mg/kg/day for 14 days before mating and throughout mating and gestation. Amlodipine maleate has been shown to prolong both the gestation period and the duration of labor in rats at this dose.

14 CLINICAL STUDIES

The antihypertensive effects of PRESTALIA have been demonstrated in two randomized controlled trials.

The highest strength of PRESTALIA (14/10 mg) was studied in a double-blind, active controlled study in hypertensive patients. A total of 837 patients with seated diastolic pressure 95 to 115 mmHg (mean baseline systolic/diastolic blood pressure was 158/101 mmHg) received treatments of PRESTALIA 14/10 mg, perindopril erbumine 16 mg, or amlodipine 10 mg once daily for 6 weeks. The mean age of the population was 51 years, 51% of patients were male, and 34% were black. Overall, 20% of the population had type 2 diabetes.

At Week 6, PRESTALIA 14/10 mg produced statistically significantly greater reductions in blood pressure than each of the monotherapies. The reductions in systolic/diastolic blood pressure with PRESTALIA 14/10 mg were 10.1/6.3 mmHg greater than with perindopril erbumine 16 mg and 3.9/2.5 mmHg greater than with amlodipine 10 mg. In black patients and in diabetic patients, treatment with PRESTALIA 14/10 mg did not provide additional antihypertensive effect beyond that achieved with use of amlodipine 10 mg.

The lowest strength of perindopril arginine/amlodipine (3.5/2.5 mg) was studied in 246 hypertensive patients. A total of 1581 patients with supine diastolic pressure 95-110 mmHg (mean baseline systolic/diastolic blood pressure was 161/101 mmHg) received treatment with perindopril arginine/amlodipine 3.5/2.5 mg, perindopril arginine 3.5 mg, perindopril arginine 5 mg, amlodipine 2.5 mg, amlodipine 5 mg, or placebo. The mean age of the population was 52 years, 47% were male, and 1% were black. No included patients had a history of diabetes.

At Week 8, PRESTALIA 3.5/2.5 mg produced statistically significantly greater reductions in blood pressure than perindopril arginine 3.5 mg and amlodipine 2.5 mg. The reduction in systolic/diastolic blood pressure with perindopril arginine/amlodipine 3.5/2.5 mg was 7.2/4.1 mmHg greater than with placebo.

16 HOW SUPPLIED/STORAGE AND HANDLING

PRESTALIA is available as white, uncoated tablets containing perindopril arginine 3.5 mg, 7 mg, or 14 mg and amlodipine 2.5 mg, 5 mg, or 10 mg for the following three combinations of perindopril arginine/amlodipine: 3.5/2.5 mg, 7/5 mg, and 14/10 mg. All three strengths are packaged in bottles of 90 tablets. Each tablet is debossed with the tablet strength.

Dose (perindopril arginine, mg/amlodipine, mg) | Imprint | NDC Code
3.5/2.5 | 3.5 imprinted on one side, 2.5 imprinted on the other side | NDC 72931-010-02
7/5 | 7/5 on one side, blank on the other | NDC 72931-011-02
14/10 | 14/10 on one side, blank on the other | NDC 72931012-02

STORAGE AND HANDLING

Storage: Store at 25°C (77°F); excursions permitted to 15-30°C (59-86°F). [See USP controlled room temperature.] Protect from moisture. Dispense in tight container (USP).

17 PATIENT COUNSELING INFORMATION

Advise the patient to read the FDA-approved patient labeling (Patient Information).

Tell female patients of childbearing age that use of drugs like perindopril that act on the renin-angiotensin system can cause serious problems in the fetus and infant, including low blood pressure, poor development of skull bones, kidney failure, and death. Discuss other treatment options with female patients planning to become pregnant. Tell women using PRESTALIA who become pregnant to notify their physician as soon as possible.

In case of a missed dose, have patients resume the usual dose at the next scheduled time.

Patient Information PRESTALIA® (pres-ta-li-a) (perindopril arginine and amlodipine) tablets

Read this Patient Information before you start taking PRESTALIA and each time you get a refill. There may be new information. This information does not take the place of talking to your doctor about your medical condition or your treatment.

What is the most important information I should know about PRESTALIA?

- PRESTALIA can cause harm or death to your unborn baby.
- Talk to your doctor about other ways to lower your blood pressure if you plan to become pregnant.
- If you become pregnant while taking PRESTALIA, tell your doctor right away. Your doctor may switch you to a different medicine to treat your high blood pressure.

What is PRESTALIA?

PRESTALIA is a prescription medicine that contains perindopril arginine, an angiotensin converting enzyme inhibitor (ACE inhibitor), and amlodipine, a calcium channel blocker.

PRESTALIA is used to treat high blood pressure (hypertension):

- when one medicine to lower your high blood pressure is not enough
- as the first medicine to lower your high blood pressure if your doctor decides you are likely to need more than one medicine

It is not known if PRESTALIA is safe and effective in children.

Who should not take PRESTALIA?

Do not take PRESTALIA if you:

- have a history of angioedema. Symptoms of angioedema may include swelling of your face, tongue or throat, trouble breathing, itching, hives or skin rash, and stomach (abdominal) pain.
- are allergic to perindopril, or any other ACE inhibitor medicine
- are allergic to amlodipine
- have diabetes and take a medicine that contains aliskiren

What should I tell my doctor before taking PRESTALIA?

Before you take PRESTALIA, tell your doctor about all of your medical conditions, including if you:

- have heart, liver or kidney problems
- have diabetes
- have been told that you have abnormal potassium levels in your blood
- are vomiting or have diarrhea
- plan to have a surgical procedure
- are pregnant or plan to become pregnant. See "What is the most important information I should know about PRESTALIA?"
- are breastfeeding or plan to breastfeed. It is not known if PRESTALIA passes into your breast milk. You and your doctor should decide if you will take PRESTALIA or breastfeed. You should not do both.

Tell your doctor about all the medicines you take, including prescription and over-the-counter medicines, vitamins, and herbal supplements. Taking PRESTALIA with other medicines can cause serious side effects.

Especially tell your doctor if you take:

- medicines for high blood pressure or heart problems
- water pills
- salt substitute
- potassium-containing medicines, potassium supplements, or salt substitutes containing potassium

Know the medicines you take. Keep a list of them to show your doctor and pharmacist when you get a new medicine.

How should I take PRESTALIA?

- Take PRESTALIA exactly as your doctor tells you.
- Take PRESTALIA 1 time each day, with or without food.
- If you miss a dose, take it as soon as you remember. If it is more than 12 hours, just take your next dose at the regular time.
- If you take too much PRESTALIA, call your doctor or go to the nearest emergency room right away.

What are the possible side effects of PRESTALIA?

PRESTALIA can cause serious side effects, including:

See "What is the most important information I should know about PRESTALIA?"

- Serious allergic reactions that can be life threatening. Stop taking PRESTALIA and get emergency medical help right away if you get any of these symptoms of a serious allergic reaction:
  - swelling of your face, lips, tongue, throat, arms, hands, legs, or feet
  - trouble swallowing
  - trouble breathing
  - stomach (abdomen) pain with or without nausea or vomiting
  People who are black and take PRESTALIA have a greater risk of having a serious allergic reaction than people who are not black and take PRESTALIA.
- Worsening of chest pain (angina) or a heart attack (myocardial infarction) can happen after you start taking or increase your dose of PRESTALIA. Get emergency help if you get worse chest pain or chest pain that does not go away.
- Low blood pressure (hypotension) is most likely to happen if you also:
  - take water pills (diuretics)
  - are on a low salt diet
  - are on kidney dialysis
  - have heart problems
  - have vomiting or diarrhea

If you feel faint or dizzy, lie down and call your doctor right away.

- Increased amount of potassium in the blood. Your doctor will check your potassium blood level during your treatment with PRESTALIA.
- Cough.
- Kidney problems. Some people with certain conditions may develop kidney problems and may need to stop treatment with PRESTALIA. Call your doctor if you get swelling in your feet, ankles, or hands, or unexplained weight gain.

The most common side effects of PRESTALIA include:

- swelling of the feet, ankles, and hands
- cough
- headache
- dizziness

Tell your doctor if you have any side effect that bothers you or that does not go away.
These are not all the possible side effects of PRESTALIA. For more information, ask your doctor or pharmacist.

Call your doctor for medical advice about side effects. You may report side effects to FDA at 1-800-FDA-1088.

How should I store PRESTALIA?

- Store PRESTALIA at room temperature between 68°F to 77°F (20°C to 25°C).
- Keep PRESTALIA in a tightly closed container and in a dry place.

Keep PRESTALIA and all medicines out of the reach of children.

General information about PRESTALIA

Medicines are sometimes prescribed for purposes other than those listed in a Patient Information leaflet. Do not use PRESTALIA for a condition for which it was not prescribed. Do not give PRESTALIA to other people, even if they have the same symptoms that you have. It may harm them.

For more information, go to www.prestalia-us.net, contact: info@adherathera.com or call 1-888-359-0394.

What is high blood pressure (hypertension)?

Blood pressure is the force in your blood vessels when your heart beats and when your heart rests. You have high blood pressure when the force is too great.

High blood pressure makes the heart work harder to pump blood through the body and causes damage to the blood vessels. PRESTALIA can help your blood vessels relax so your blood pressure is lower. Medicines that lower your blood pressure lower your chance of having a stroke or heart attack.

What are the ingredients in PRESTALIA?

Active ingredients: perindopril arginine and amlodipine besylate
Inactive ingredients: lactose, microcrystalline cellulose, colloidal silicon dioxide, and magnesium stearate

This Patient Information has been approved by the U.S. Food and Drug Administration.

Marketed by:
Adhera Therapeutics, Inc.
Durham, NC 27703

Issued: 08/2019

PRESTALIA® is a registered trademark of Biofarma used by Adhera Therapeutics, Inc. under license from Biofarma. Adhera Therapeutics and the Adhera Therapeutics logo are trademarks of Adhera Therapeutics, Inc.

PRINCIPAL DISPLAY PANEL - 3.5 mg/2.5 mg Tablet Bottle Label

90 Tablets
NDC 72931-010-02

Prestalia®

(perindopril arginine and
amlodipine) Tablets

3.5 mg/2.5 mg

Rx ONLY
Keep out of reach of children

adhera
THERAPEUTICS

PRINCIPAL DISPLAY PANEL - 7 mg/5 mg Tablet Bottle Label

90 Tablets
NDC 72931-011-02

Prestalia®

(perindopril arginine and
amlodipine) Tablets

7 mg/5 mg

Rx ONLY
Keep out of reach of children

adhera
THERAPEUTICS

PRINCIPAL DISPLAY PANEL - 14 mg/10 mg Tablet Bottle Label

90 Tablets
NDC 72931-012-02

Prestalia®

(perindopril arginine and
amlodipine) Tablets

14 mg/10 mg

Rx ONLY
Keep out of reach of children

adhera
THERAPEUTICS